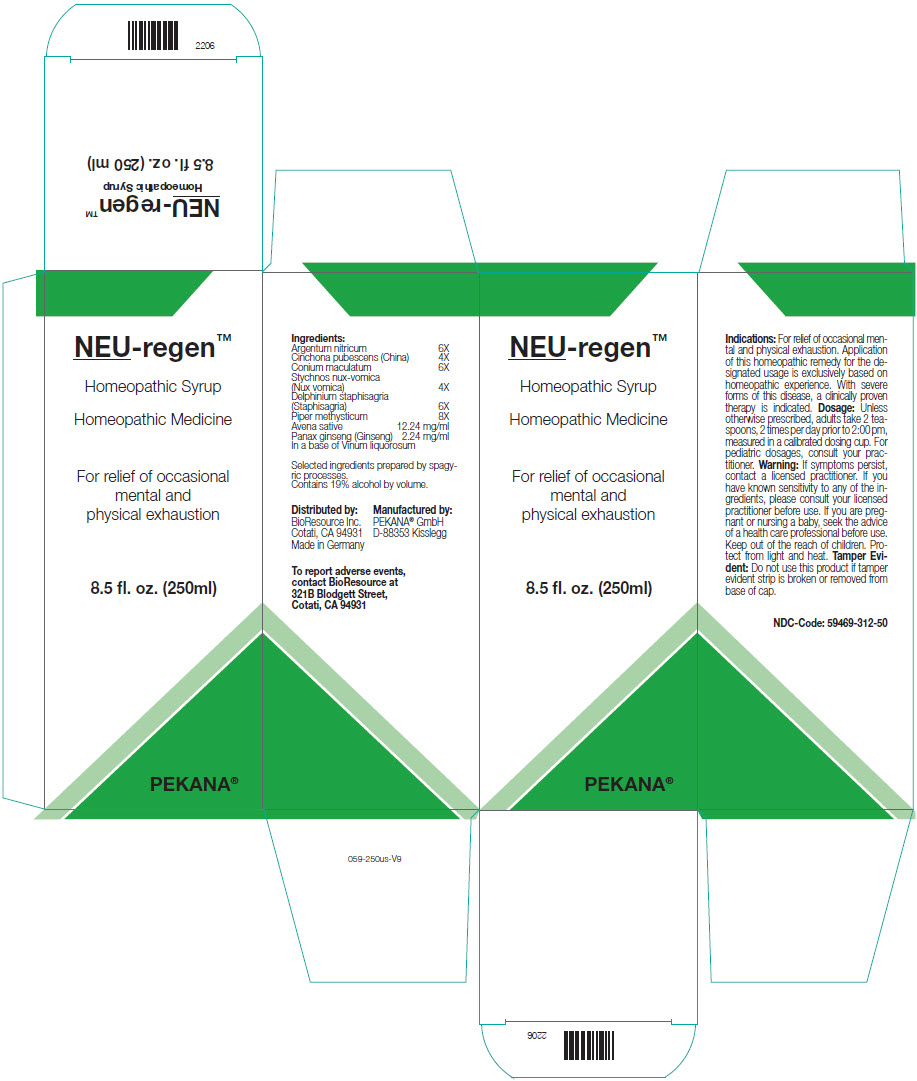 DRUG LABEL: NEU-regen
NDC: 59469-312 | Form: SYRUP
Manufacturer: PEKANA Naturheilmittel GmbH
Category: homeopathic | Type: HUMAN OTC DRUG LABEL
Date: 20230111

ACTIVE INGREDIENTS: SILVER NITRATE 6 [hp_X]/250 mL; CINCHONA OFFICINALIS BARK 4 [hp_X]/250 mL; CONIUM MACULATUM FLOWERING TOP 6 [hp_X]/250 mL; STRYCHNOS NUX-VOMICA SEED 4 [hp_X]/250 mL; DELPHINIUM STAPHISAGRIA SEED 6 [hp_X]/250 mL; PIPER METHYSTICUM ROOT 8 [hp_X]/250 mL; AVENA SATIVA FLOWERING TOP 3061 mg/250 mL; ASIAN GINSENG 561 mg/250 mL
INACTIVE INGREDIENTS: WATER; ALCOHOL

NEU-regen™

ACTIVE INGREDIENT

Ingredients:
Argentum nitricum | 6X
Cinchona pubescens (China) | 4X
Conium maculatum | 6X
Stychnos nux-vomica (Nux vomica) | 4X
Delphinium staphisagria (Staphisagria) | 6X
Piper methysticum | 8X
Avena sative | 12.24 mg/ml
Panax ginseng (Ginseng) | 2.24 mg/ml
In a base of Vinum liquorosum

Selected ingredients prepared by spagyric processes.

INACTIVE INGREDIENT

Contains 19% alcohol by volume.

Indications

PURPOSE

For relief of occasional mental and physical exhaustion. Application of this homeopathic remedy for the designated usage is exclusively based on homeopathic experience. With severe forms of this disease, a clinically proven therapy is indicated.

Dosage

Unless otherwise prescribed, adults take 2 teaspoons, 2 times per day prior to 2:00 pm, measured in a calibrated dosing cup. For pediatric dosages, consult your practitioner.

Warning

ASK DOCTOR

If symptoms persist, contact a licensed practitioner. If you have known sensitivity to any of the ingredients, please consult your licensed practitioner before use. If you are pregnant or nursing a baby, seek the advice of a health care professional before use.

Keep out of the reach of children.

STORAGE AND HANDLING

Protect from light and heat.

Tamper Evident

Do not use this product if tamper evident strip is broken or removed from base of cap.

QUESTIONS

To report adverse events, contact BioResource at 321B Blodgett Street, Cotati, CA 94931

Distributed by:
BioResource Inc.
Cotati, CA 94931

Manufactured by:
PEKANA® GmbH
D-88353 Kisslegg

PRINCIPAL DISPLAY PANEL - 250 ml Bottle Box

NEU-regen™

Homeopathic Syrup

Homeopathic Medicine

For relief of occasional
mental and
physical exhaustion

8.5 fl. oz. (250ml)

PEKANA®